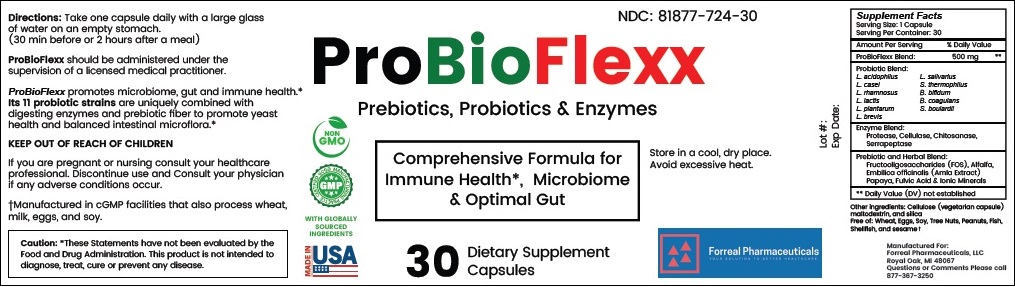 DRUG LABEL: ProBioFlexx
NDC: 81877-724 | Form: CAPSULE
Manufacturer: Forreal Pharmaceuticals, LLC 
Category: other | Type: DIETARY SUPPLEMENT
Date: 20240517

ACTIVE INGREDIENTS: LACTOBACILLUS ACIDOPHILUS 2 mg/1 1; LACTICASEIBACILLUS CASEI 2 mg/1 1; LACTICASEIBACILLUS RHAMNOSUS 2 mg/1 1; BIFIDOBACTERIUM ANIMALIS LACTIS 2 mg/1 1; LACTIPLANTIBACILLUS PLANTARUM 2 mg/1 1; LEVILACTOBACILLUS BREVIS 2 mg/1 1; LIGILACTOBACILLUS SALIVARIUS 2 mg/1 1; STREPTOCOCCUS THERMOPHILUS 2 mg/1 1; BIFIDOBACTERIUM BIFIDUM 2 mg/1 1; BACILLUS COAGULANS 20 mg/1 1; SACCHAROMYCES CEREVISIAE 9 mg/1 1; ASPERGILLUS FLAVUS VAR. ORYZAE PROTEASE 22 mg/1 1; BACILLUS SUBTILIS 92 mg/1 1; SERRAPEPTASE 10 mg/1 1; ALFALFA 42 mg/1 1; PAPAYA 93 mg/1 1
INACTIVE INGREDIENTS: FULVIC ACID; CALCIUM; MAGNESIUM; MANGANESE

ProBioFlexx

STATEMENT OF IDENTITY

Supplement Facts

Serving Size: 1 Capsule
Serving Per Container: 30

Amount Per Serving % Daily Value

ProBioFlexx Blend: 500 mg **

Probiotic Blend:

L. acidophilus
L. casei
L. rhamnosus
L. lactis
L. plantarum
L. brevis

L. salivarius
S. thermophilus
B. bifidum
B. coagulans
S. boulardii

Enzyme Blend:
Protease, Cellulase, Chitosanase, Serrapeptase

Prebiotic and Herbal Blend:
Fructooligosaccharides (FOS), Alfalfa,
Embilica officinalis (Amla Extract)
Papaya, Fulvic Acid & Ionic Minerals

** Daily Value (DV) not established

Other ingredients: Cellulose (vegetarian capsule) maltodextrin, and silica

Free of: Wheat, Eggs, Soy, Tree Nuts, Peanuts, Fish, Shellfish, and sesame ✝

Forreal Pharmaceuticals, LLC
Royal Oak, MI
Phone: 877-367-3250

Directions:

Take one capsule daily with a large glass of water on an empty stomach. (30 min before or 2 hours after a meal)

SAFE HANDLING

ProBioFlexx should be administered under the supervision of a licensed medical practitioner.

HOW SUPPLIED HEALTH CLAIM

ProBioFlexx promotes microbiome, gut and immune health. Its 11 probiotic strains are uniquely combined with Candida-digesting enzymes and prebiotic fiber to promote yeast health and balanced intestinal microflora.

KEEP OUT OF REACH OF CHILDREN

If you are pregnant or nursing consult you Healthcare professional and discontinue use and Consult your physician if any adverse conditions occur.

†Manufactured in cGMP facilities that also process wheat, milk, eggs, and soy.

Caution: These Statements have not been evaluated by the Food and Drug Administration. This product is not intended to diagnose, treat, cure or prevent any disease.

PRINCIPAL DISPLAY PANEL

NDC: 81877-724-30

ProBioFlexx

Prebiotics, Probiotics & Enzymes

Comprehensive Formula for
Immune Health*, Microbiome
& Optimal Gut

Store in a cool, dry place.
Avoid excessive heat.

30

Dietary Supplement
Capsules

Forreal Pharmaceuticals
YOUR SOLUTION TO BETTER HEALTHCARE.